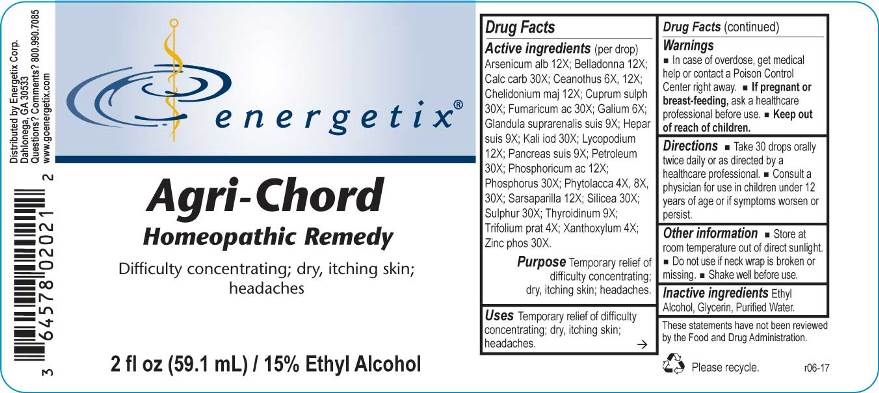 DRUG LABEL: Agri-Chord
NDC: 64578-0055 | Form: LIQUID
Manufacturer: Energetix Corp
Category: homeopathic | Type: HUMAN OTC DRUG LABEL
Date: 20170713

ACTIVE INGREDIENTS: ARSENIC TRIOXIDE 12 [hp_X]/1 mL; ATROPA BELLADONNA 12 [hp_X]/1 mL; OYSTER SHELL CALCIUM CARBONATE, CRUDE 30 [hp_X]/1 mL; CEANOTHUS AMERICANUS LEAF 6 [hp_X]/1 mL; CHELIDONIUM MAJUS 12 [hp_X]/1 mL; CUPRIC SULFATE 30 [hp_X]/1 mL; FUMARIC ACID 30 [hp_X]/1 mL; GALIUM APARINE 6 [hp_X]/1 mL; SUS SCROFA ADRENAL GLAND 9 [hp_X]/1 mL; PORK LIVER 9 [hp_X]/1 mL; POTASSIUM IODIDE 30 [hp_X]/1 mL; LYCOPODIUM CLAVATUM SPORE 12 [hp_X]/1 mL; SUS SCROFA PANCREAS 9 [hp_X]/1 mL; KEROSENE 30 [hp_X]/1 mL; PHOSPHORIC ACID 12 [hp_X]/1 mL; PHOSPHORUS 30 [hp_X]/1 mL; PHYTOLACCA AMERICANA ROOT 4 [hp_X]/1 mL; SMILAX REGELII ROOT 12 [hp_X]/1 mL; SILICON DIOXIDE 30 [hp_X]/1 mL; SULFUR 30 [hp_X]/1 mL; THYROID, BOVINE 9 [hp_X]/1 mL; TRIFOLIUM PRATENSE FLOWER 4 [hp_X]/1 mL; ZANTHOXYLUM AMERICANUM BARK 4 [hp_X]/1 mL; ZINC PHOSPHIDE 30 [hp_X]/1 mL
INACTIVE INGREDIENTS: WATER; ALCOHOL; GLYCERIN

Drug Facts:

ACTIVE INGREDIENTS:

Arsenicum Album 12X; Belladonna 12X; Calcarea Carbonica 30X; Ceanothus Americanus 6X, 12X; Chelidonium Majus 12X; Cuprum Sulphuricum 30X; Fumaricum Acidum 30X; Galium Aparine 6X; Glandula Suprarenalis Suis 9X; Hepar Suis 9X; Kali Iodatum 30X; Lycopodium Clavatum 12X; Pancreas Suis 9X; Petroleum 30X; Phosphoricum Acidum 12X; Phosphorus 30X; Phytolacca Decandra 4X, 8X, 30X; Sarsaparilla (Smilax Regelii) 12X; Silicea 30X; Sulphur 30X; Thyroidinum (Bovine) 9X; Trifolium Pratense 4X; Xanthoxylum Fraxineum 4X; Zincum Phosphoratum 30X.

PURPOSE:

Temporary relief difficulty concentrating; dizziness; dry, itching skin; headaches.

WARNINGS:

Keep out of reach of children. In case of overdose, get medical help or contact a Poison Control Center right away.

If pregnant or breast feeding, ask a health professional before use.

Store in cool, dry place out of direct sunlight.

Do not use if neck wrap is broken or missing.

Keep out of reach of children. In case of overdose, get medical help or contact a Poison Control Center right away.

DIRECTIONS:

Take 30 drops orally twice daily or as directed by a healthcare professional.

Consult a physician for use in children under 12 years of age or if symptoms worsen or persist.

USES:

Temporary relief of difficulty concentrating; dry, itching skin; headaches.

INACTIVE INGREDIENTS:

Ethyl Alcohol, Glycerin, Purified Water

QUESTIONS:

Distributed by

Energetix Corp.

Dahlonega, GA 30533

Questions? 800.990.7085

PACKAGE LABEL DISPLAY:

energetix

Agri-Chord

Homeopathic Remedy

Difficulty concentrating; dry, itching skin;

headaches

2 fl oz (59.1 mL)